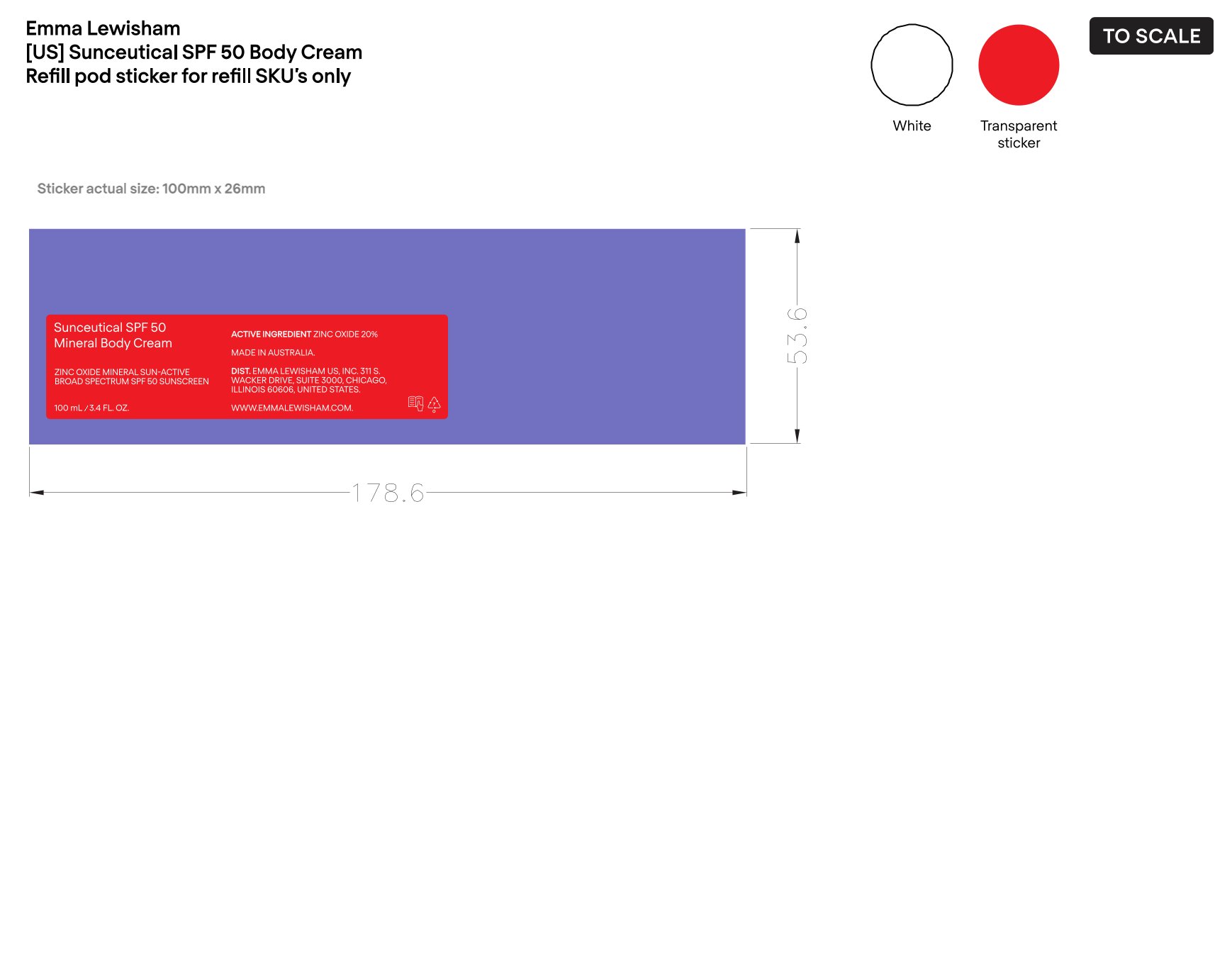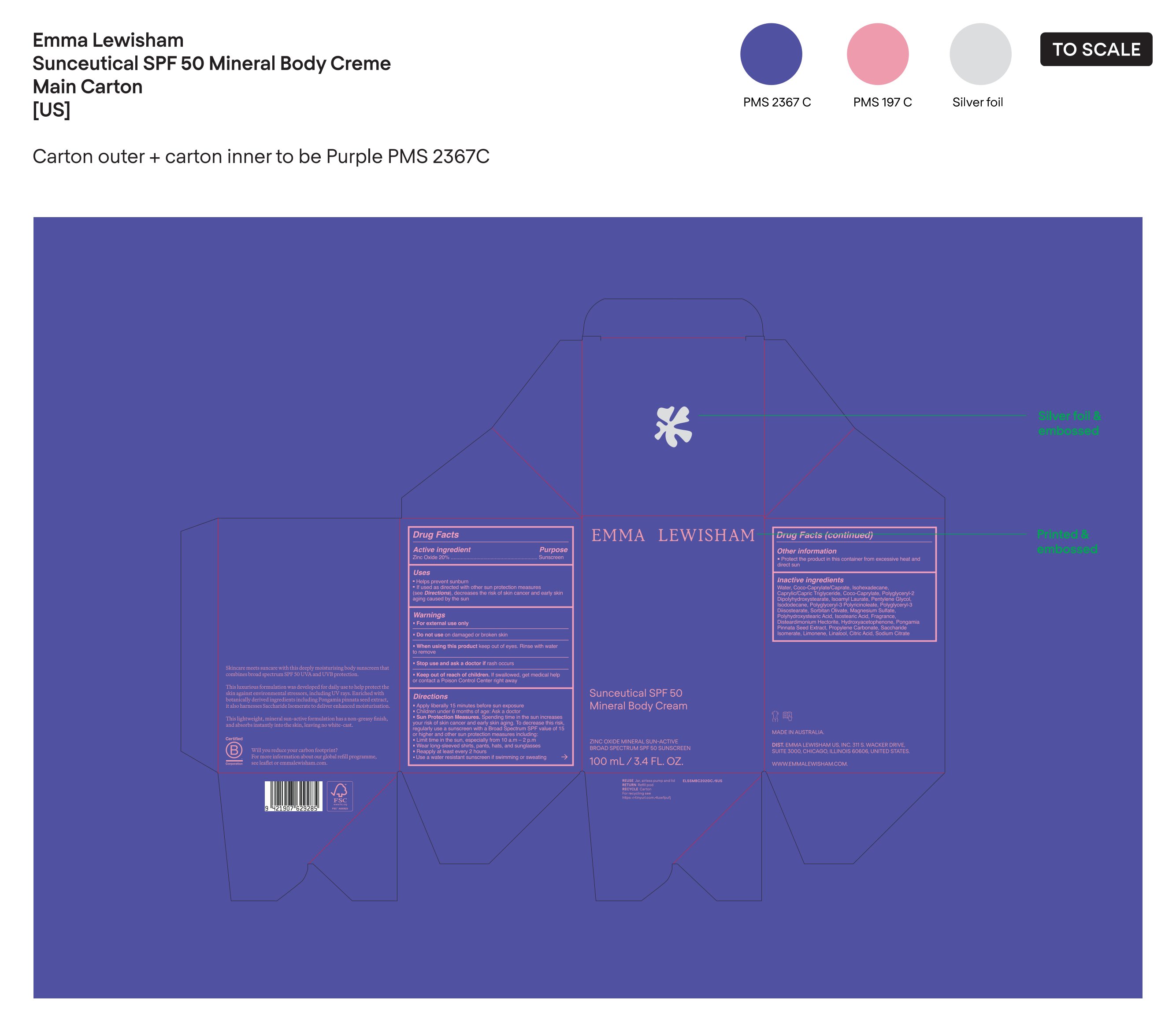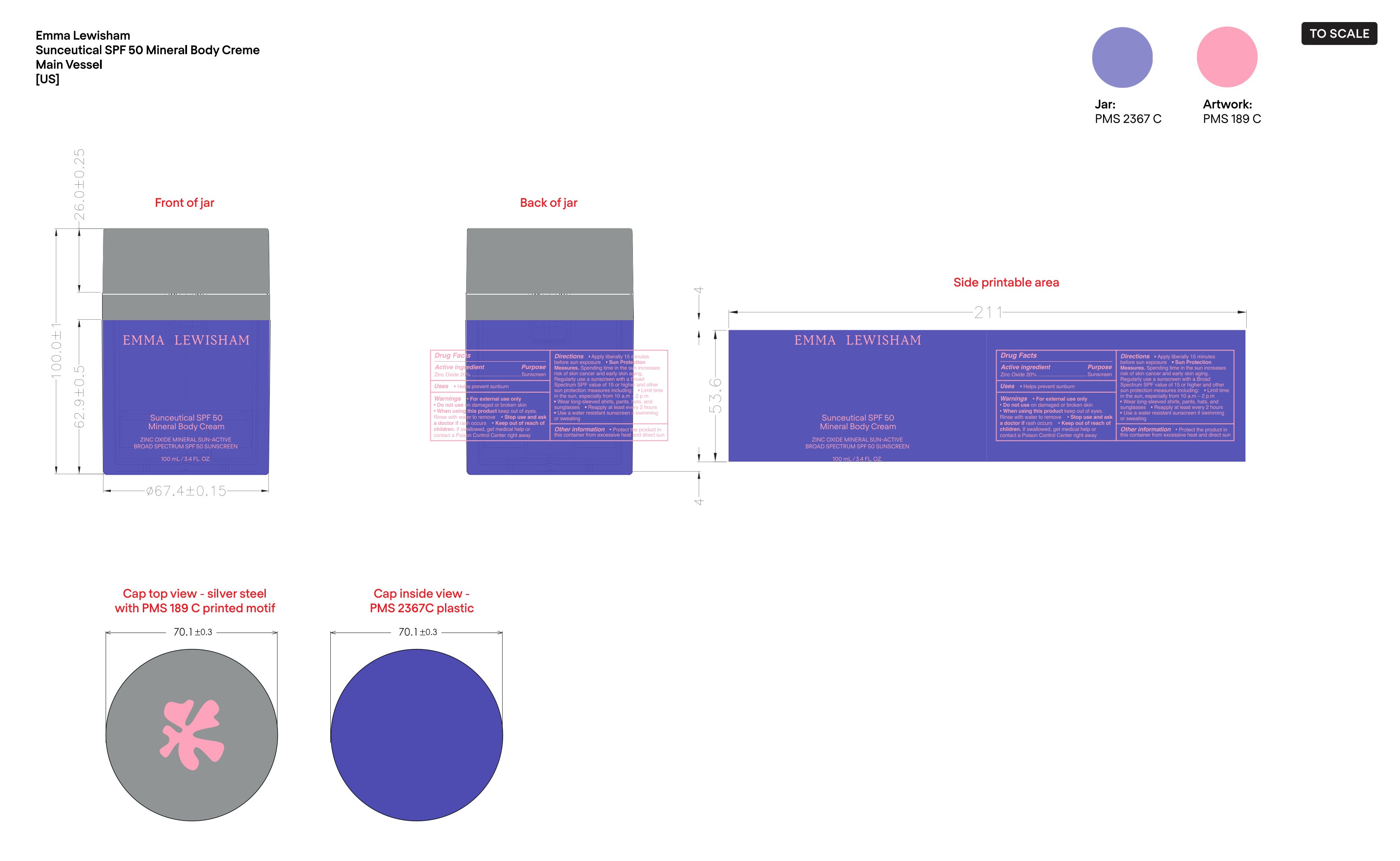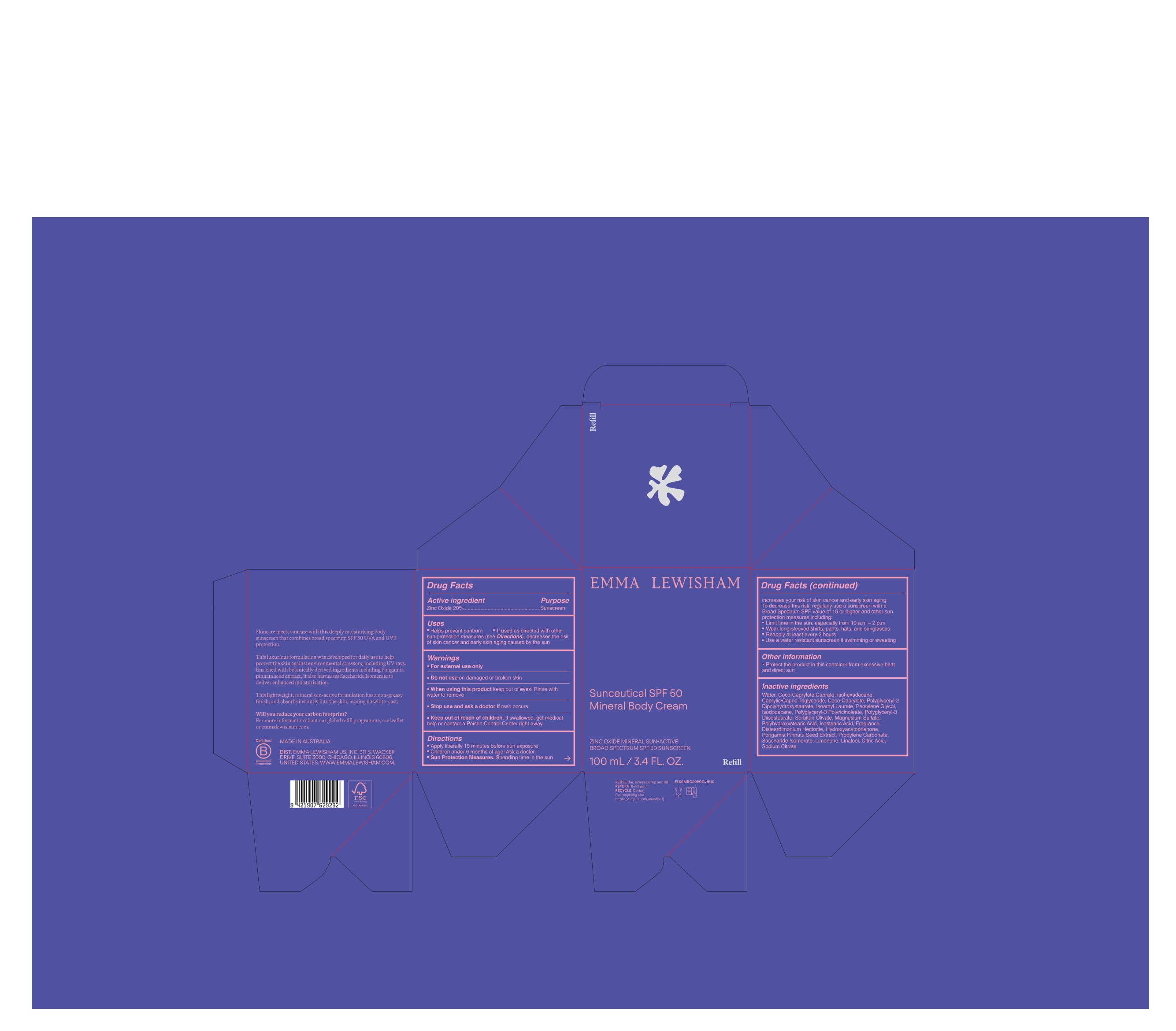 DRUG LABEL: EMMA LEWISHAM Sunceutical SPF 50 Mineral Body Cream
NDC: 84981-003 | Form: LOTION
Manufacturer: EMMA LEWISHAM US, INC.
Category: otc | Type: HUMAN OTC DRUG LABEL
Date: 20250205

ACTIVE INGREDIENTS: ZINC OXIDE 20 g/100 mL
INACTIVE INGREDIENTS: POLYGLYCERYL-3 PENTARICINOLEATE; ISOCYCLEMONE E; LEMON TERPENES; HYDROXYACETOPHENONE; PONGAMIA PINNATA SEED; PROPYLENE CARBONATE; SACCHARIDE ISOMERATE; ISOHEXADECANE; CAPRYLIC/CAPRIC TRIGLYCERIDE; COCO-CAPRYLATE/CAPRATE; SODIUM CITRATE; POLYGLYCERYL-3 DIISOSTEARATE; POLYHYDROXYSTEARIC ACID (2300 MW); WATER; COCO-CAPRYLATE; ISODODECANE; MAGNESIUM SULFATE; HEXAMETHYLINDANOPYRAN; LINALYL ACETATE; DISTEARDIMONIUM HECTORITE; PENTYLENE GLYCOL; POLYGLYCERYL-2 DIPOLYHYDROXYSTEARATE; ISOAMYL LAURATE; SORBITAN OLIVATE; ISOSTEARIC ACID; LIMONENE, (+)-; LINALOOL; CITRIC ACID

Drug Facts

Active Ingredient

Zinc Oxide 20%

Purpose

Sunscreen

Uses

- Helps prevent sunburn
- If used as directed with other sun protection measures (see Directions), decreases the risk of Skin cancer and early skin aging caused by the sun

Warnings

- For external use only
- Do not use on damaged or broken skin
- When using this product keep out of eyes. Rinse with water to remove
- Stop use and ask a doctor if rash occurs.

- Keep out of reach of children. If swallowed, get medical help or contact a Poison Control Center right away

Directions

- Apply liberally 15 minutes before sun exposure
- Children under 6 months of age: Ask a doctor
- Sun Protection Measures. Spending time in the sun increases your risk of skin cancer and early skin aging. To decrease this risk, regularly use a sunscreen with a Broad spectrum SPF value of 15 or higher and other sun protection measures including:
- Limit time in the sun, especially from 10 a.m. -2 p.m.
- Wear long-sleeved shirts, pants, hats, and sunglasses
- Reapply at least every 2 hours
- Use a water resistant sunscreen if swimming or sweating

Other information

- Protect the product in this container from excessive heat and direct sun

Inactive Ingredients

Water, Coco-Caprylate/Caprate, Isohexadecane, Caprylic/Capric Triglyceride, Coco-Caprylate, Polyglyceryl-2 Dipolyhydroxystearate, Isoamyl Laurate, Pentylene Glycol, Isododecane, Polyglyceryl-3 Polyricinoleate, Polyglyceryl-3 Diisostearate, Sorbitan Olivate, Magnesium Sulfate, Polyhydroxystearic Acid, Isostearic Acid, Fragrance, Disteardimonium Hectorite, Hydroxyacetophenone, Pongamia Pinnata Seed Extract, Propylene Carbonate, Saccharide Isomerate, Limonene, Linalool, Citric Acid, Sodium Citrate

PRINCIPAL DISPLAY PANEL

EMMA LEWISHAM

Sunceutical SPF 50 Mineral Body Cream

ZINC OXIDE MINERAL SUN-ACTIVE

BROAD SPECTRUM SPF 50 SUNSCREEN

100 mL/3.4 FL. OZ.

PACKAGE LABEL

Sunceutical SPF 50 Mineral Body Cream

ZINC OXIDE MINERAL SUN-ACTIVE

BROAD SPECTRUM SPF 50 SUNSCREEN

100 mL/3.4 FL. OZ.